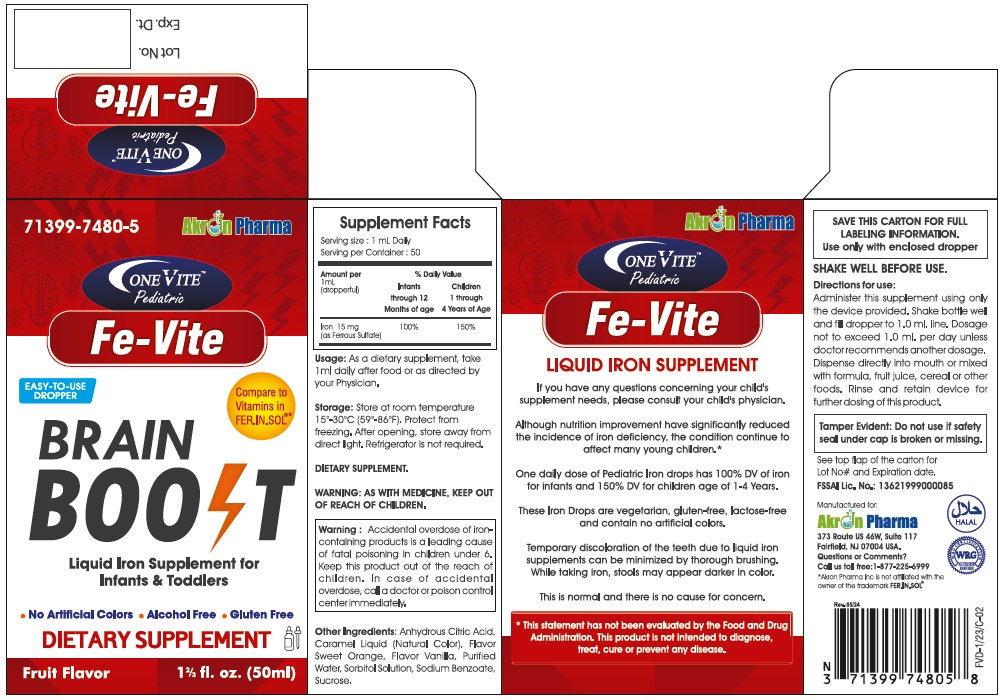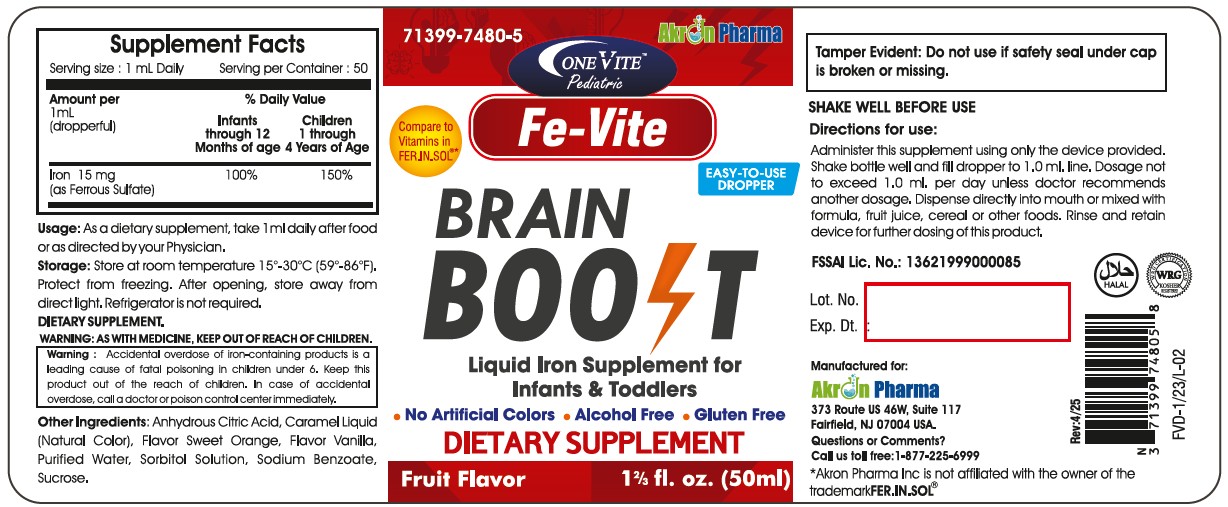 DRUG LABEL: FE-Vite Iron Oral Solution
NDC: 71399-7480 | Form: SOLUTION
Manufacturer: Akron Pharma
Category: other | Type: DIETARY SUPPLEMENT
Date: 20250505

ACTIVE INGREDIENTS: FERROUS SULFATE 15 mg/1 mL
INACTIVE INGREDIENTS: SUCROSE; SORBITOL; ANHYDROUS CITRIC ACID; SODIUM BENZOATE; CARAMEL; WATER

OneVITE Pediatric
Fe-Vite
Brain Boost
Drops

STATEMENT OF IDENTITY

Supplement Facts

Serving Size: 1 mL Daily

Serving per container: 50

Amount per 1 mL (dropperful) % Daily Value

Infants through 12 Months of age Children 1 through 4 years of age

Iron (as Ferrous Sulfate) 15 mg 100% 150%

HEALTH CLAIM

Although nutrition improvement have significantly reduced the incidence of iron deficiency, the condition continue to affect many young children.*

One daily dose of Pediatric Iron drops has 100% DV of iron for infants and 150% DV for children age of 1-4 Years.

* This statement has not been evaluated by the Food and Drug Administration. This product is not intended to diagnose, treat, cure, or prevent any disease.

SAFE HANDLING WARNING

Storage: Store at room temperature 15º -30ºC(59º - 86ºF). Protect from freezing. After opening, store away from direct light. Refrigerator is not required.

WARNINGS

WARNING: Accidental overdose of iron-containing products is a leading cause of fatal poisoning in children under 6. Keep this product out of the reach of children. In case of accidental overdose, call a doctor or poison control center immediately.

PRECAUTIONS

SHAKE WELL BEFORE USE.

DOSAGE AND ADMINISTRATION

Directions for use:

Administer this supplement using only the device provided. Shake bottle well and fill dropper to 1.0 ml. line. Dosage not to exceed 1.0 ml. per day unless doctor recommends another dosage. Dispense directly into mouth or mixed with formula, fruit juice, cereal, or other foods. Rinse and retain device for further dosing of this product.